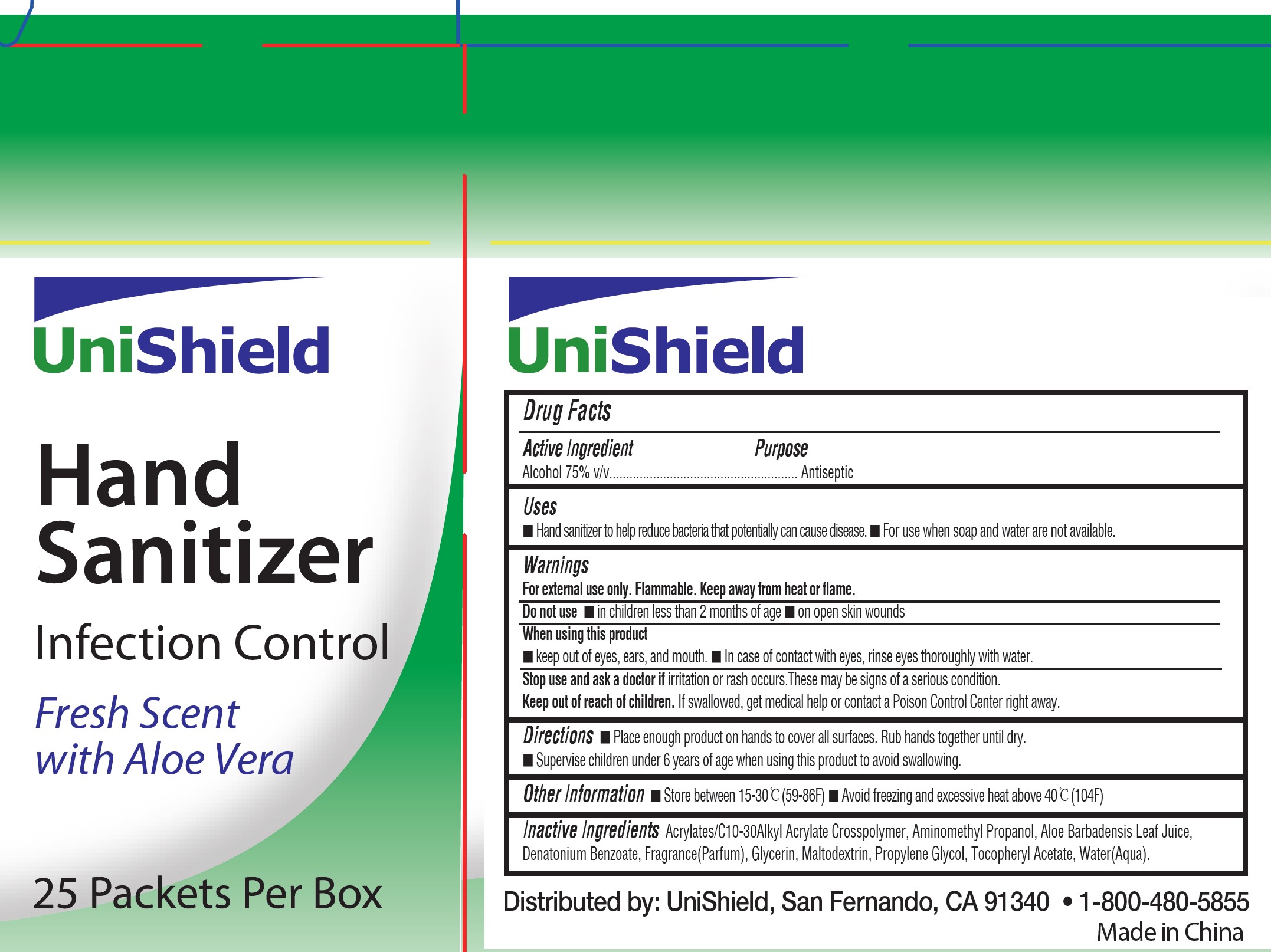 DRUG LABEL: Unishield Hand Sanitizer
NDC: 49314-0004 | Form: GEL
Manufacturer: Unishield
Category: otc | Type: HUMAN OTC DRUG LABEL
Date: 20250924

ACTIVE INGREDIENTS: ALCOHOL 75 mL/100 mL
INACTIVE INGREDIENTS: WATER; GLYCERIN; PROPYLENE GLYCOL; ACRYLATES/C10-30 ALKYL ACRYLATE CROSSPOLYMER (60000 MPA.S); .ALPHA.-TOCOPHEROL ACETATE; AMINOMETHYLPROPANOL; DENATONIUM BENZOATE; MALTODEXTRIN; ALOE

49314-0004 Unishield sanitizer

Active ingredient

Ethyl Alcohol, 75% v/v

Purpose Antiseptic

Uses

- Hand sanitizer to help reduce bacteria that potentially can cause disease
- For use when soap and water are not available

Warnings

For external use only.

Flammable, keep away from heat or flame.

Do not use

- In children less than two months of age
- On open skin wounds

When using this product:

- Keep out of eyes, ears, and mouth
- In case of contact with eyes, rinse eyes throughly with water

Stop use and ask a doctor if irritation or rash occurs. They may be signs of a serious condition.

Keep out of reach of children. If swallowed, get medical help or contact a Poison Control Center right away.

Directions

- Place enough product on hands to cover all surfaces. Rub hands together until dry.
- Supervise children under 6 years of age when using this product to avoid swallowing.

Other information

- Store between 15-30C (59-86F)
- Avoid freezing and excessive heat above 40C (104F)

Inactive ingredients

acrylates/ C10-C30 alkyl acrylate crossploymer, aminomethyl propanol, aloe barbadensis leaf jiuce,denatonium benzoate,fragrance, glycerin,maltodextrin, propylene glycol, tocopheryl acetate, water